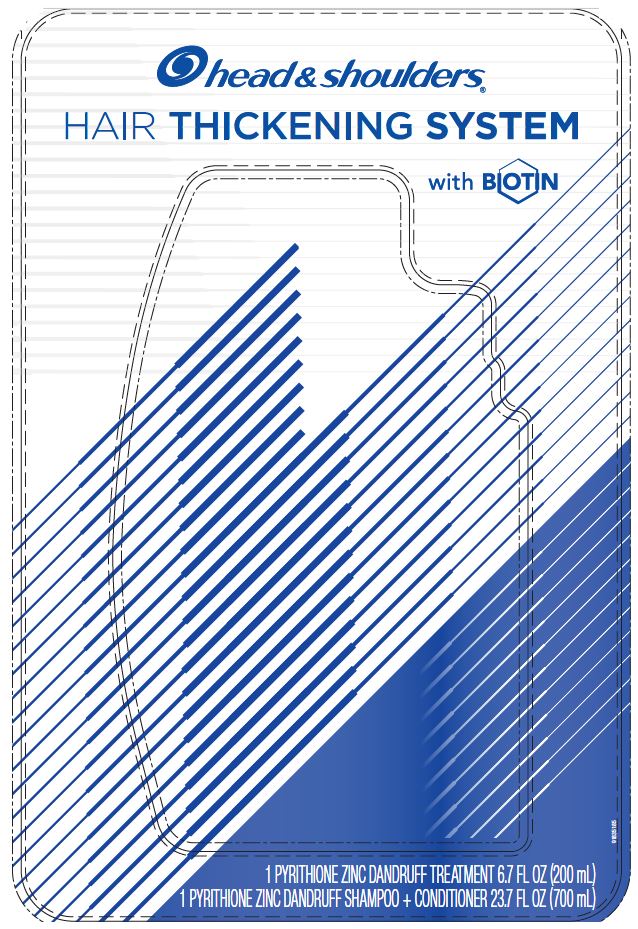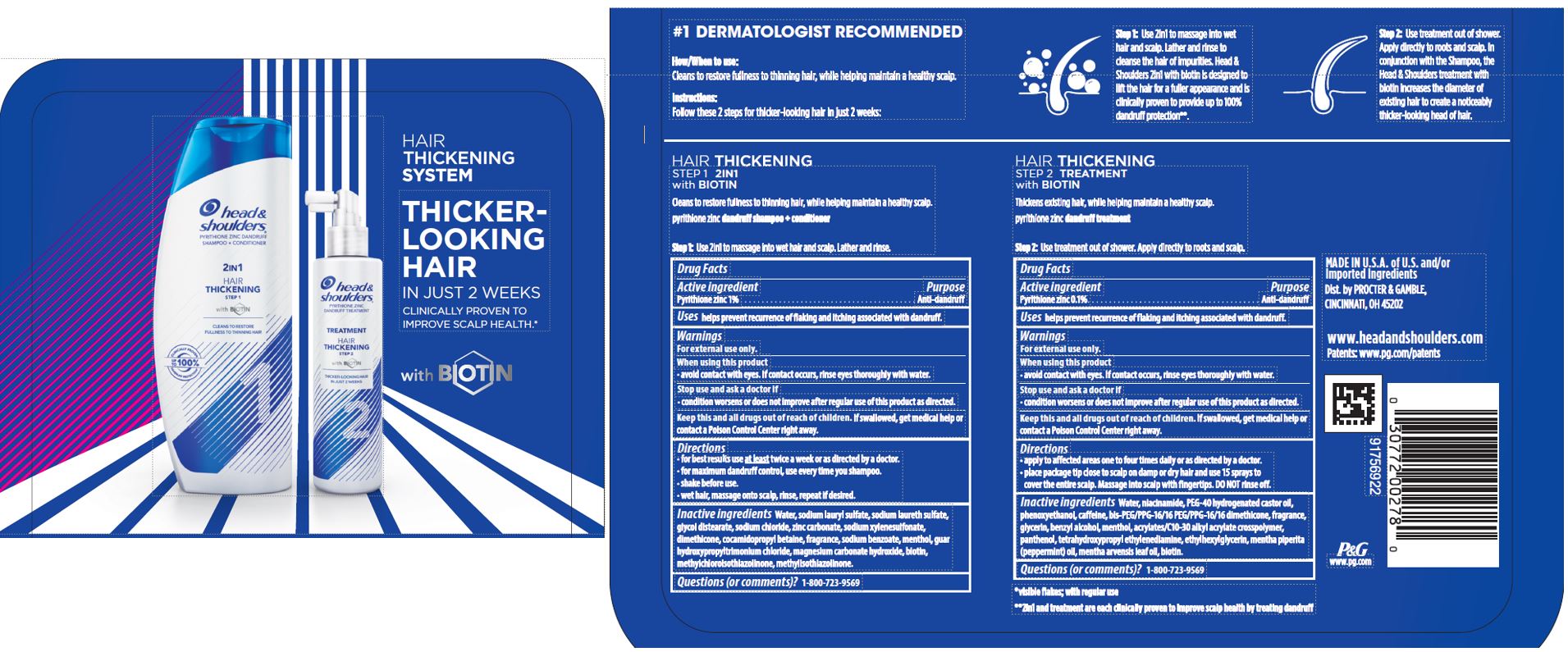 DRUG LABEL: Head and Shoulders Hair Thickening System
NDC: 69423-593 | Form: KIT | Route: TOPICAL
Manufacturer: The Procter & Gamble Manufacturing Company
Category: otc | Type: HUMAN OTC DRUG LABEL
Date: 20211202

ACTIVE INGREDIENTS: PYRITHIONE ZINC 1 g/100 mL; PYRITHIONE ZINC 0.1 g/100 mL
INACTIVE INGREDIENTS: MENTHOL; COCAMIDOPROPYL BETAINE; SODIUM LAURYL SULFATE; GUAR HYDROXYPROPYLTRIMONIUM CHLORIDE (1.7 SUBSTITUENTS PER SACCHARIDE); WATER; SODIUM LAURETH-3 SULFATE; ZINC CARBONATE; GLYCOL DISTEARATE; SODIUM XYLENESULFONATE; DIMETHICONE; SODIUM CHLORIDE; SODIUM BENZOATE; MAGNESIUM CARBONATE HYDROXIDE; METHYLCHLOROISOTHIAZOLINONE; METHYLISOTHIAZOLINONE; BIOTIN; EDETOL; WATER; CARBOMER INTERPOLYMER TYPE A (55000 CPS); BIOTIN; BIS-PEG/PPG-16/16 PEG/PPG-16/16 DIMETHICONE; CAFFEINE; ETHYLHEXYLGLYCERIN; PHENOXYETHANOL; BENZYL ALCOHOL; GLYCERIN; MENTHA ARVENSIS LEAF OIL; PEPPERMINT OIL; MENTHOL, UNSPECIFIED FORM; PANTHENOL; NIACINAMIDE; POLYOXYL 40 HYDROGENATED CASTOR OIL

Head and Shoulders® Hair Thickening System

Active ingredient

Pyrithione zinc 1%

Hair Thickening

Step 1 2in1

with BIOTIN

Cleans to restore fullness to thinning hair, while helping maintain a healthy scalp.

pyrithione zinc dandruff shampoo + conditioner

Step 1: Use 2in1 to massage into wet hair and scalp. Lather and rinse.

Drug Facts

Purpose

Anti-dandruff

Uses

helps prevent recurrence of flaking and itching associated with dandruff.

Warnings

For external use only.

When using this product

- avoid contact with eyes. If contact occurs, rinse eyes thoroughly with water.

Stop use and ask a doctor if

- condition worsens or does not improve after regular use of this product as directed.

KEEP OUT OF REACH OF CHILDREN

Keep this and all drugs out of reach of children.

If swallowed, get medical help or contact a Poison Control Center right away.

Directions

- for best results use at least twice a week or as directed by a doctor.
- for maximum dandruff control, use every time you shampoo
- shake before use.
- wet hair, massage onto scalp, rinse, repeat if desired.

Inactive ingredients

Water, sodium lauryl sulfate, sodium laureth sulfate, glycol distearate, sodium chloride, zinc carbonate, sodium xylenesulfonate, dimethicone, cocamidopropyl betaine, fragrance, sodium benzoate, menthol, guar hydroxypropyltrimonium chloride,magnesium carbonate hydroxide, biotin, methylchloroisothiazolinone, methylisothiazolinone.

Questions (or comments)?

1-800-723-9569

Hair Thickening

Step 2 Treatment

with BIOTIN

Thickens existing hair, while helping maintain a healthy scalp.

pyrithione zinc dandruff treatment

Step 2: Use treatment out of shower. Apply directly to roots and scalp.

Drug Facts

Active ingredient

Pyrithione zinc 0.1%

Purpose

Anti-dandruff

Uses

helps prevent recurrence of flaking and itching associated with dandruff.

Warnings

For external use only.

When using this product

- avoid contact with eyes. If contact occurs, rinse eyes thoroughly with water.

Stop use and ask a doctor if

- condition worsens or does not improve after regular use of this product as directed.

KEEP OUT OF REACH OF CHILDREN

Keep this and all drugs out of reach of children.

If swallowed, get medical help or contact a Poison Control Center right away.

Directions

- apply to affected areas one to four times daily or as directed by a doctor.
- place package tip close to scalp on damp or dry hair and use 15 sprays to cover the entire scalp. Massage into scalp with fingertips. DO NOT rinse off.

Inactive ingredients

Water, niacinamide, PEG-40 hydrogenated castor oil, phenoxyethanol, caffeine, bis-PEG/PPG-16/16 PEG/PPG-16/16 dimethicone, fragrance, glycerin, benzyl alcohol, menthol, acrylates/C10-30 alkyl acrylate crosspolymer, panthenol, tetrahydroxypropyl ethylenediamine, ethylhexylglycerin, mentha piperita (peppermint) oil, mentha arvensis leaf oil, biotin.

Questions (or comments)?

1-800-723-9569

Dist. by PROCTER & GAMBLE,
CINCINNATI, OH 45202

PRINCIPAL DISPLAY PANEL - Kit Package

head &
shoulders®

HAIR THICKENING SYSTEM

WITH BIOTIN

head & shoulders

pyrithione zinc dandruff shampoo + conditioner

2in1 Hair Thickening Step 1

with Biotin

23.7 FL OZ (700 mL)

head &
shoulders®

pyrithione zinc dandruff treatment

Treatment

Hair Thickening Step 2

with Biotin

6.7 FL OZ (200 mL)